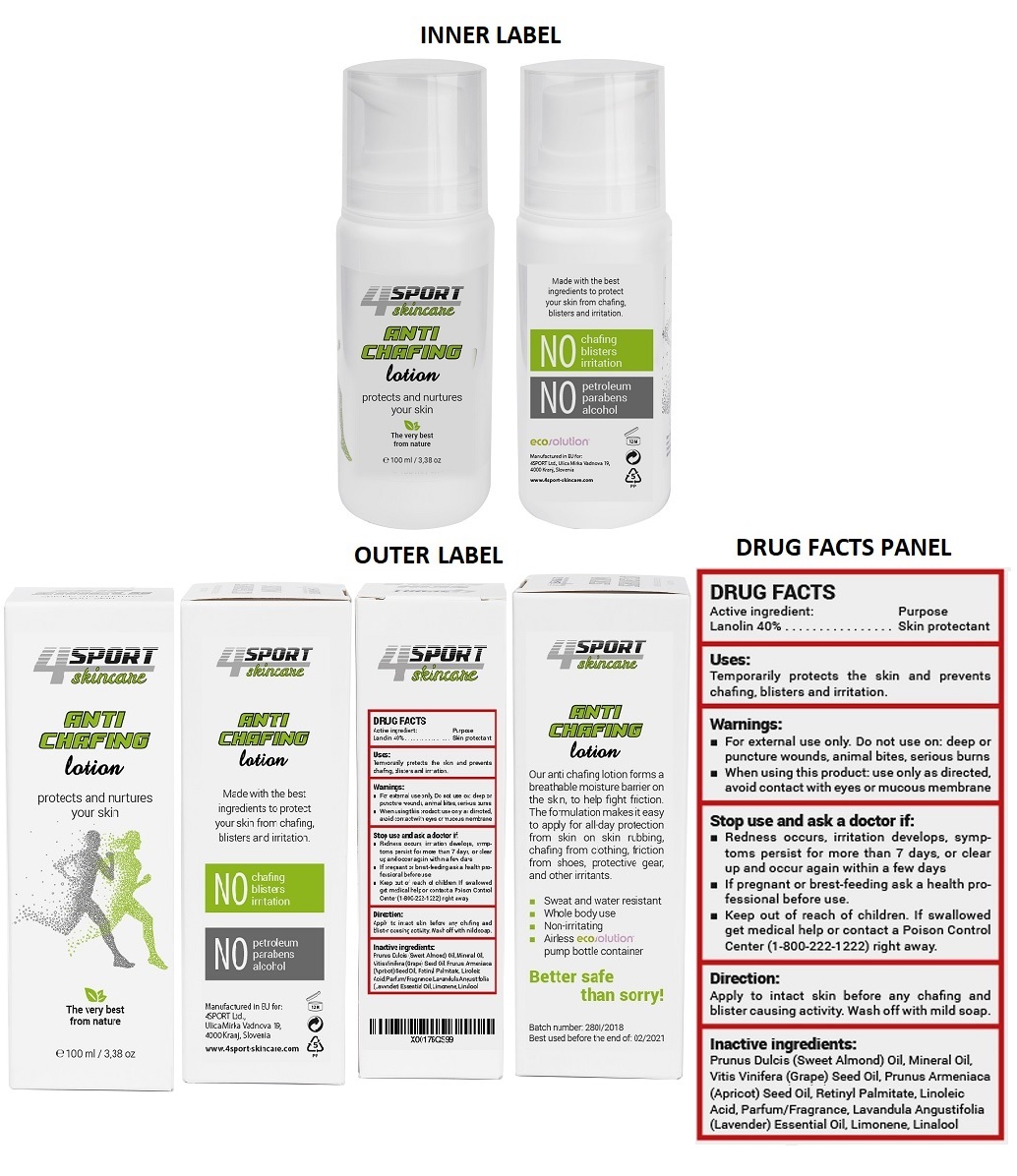 DRUG LABEL: 4sport skincare anti chafing
NDC: 71289-101 | Form: LOTION
Manufacturer: 4sport D.o.o.
Category: otc | Type: HUMAN OTC DRUG LABEL
Date: 20180625

ACTIVE INGREDIENTS: LANOLIN 40 g/100 mL
INACTIVE INGREDIENTS: ALMOND OIL; MINERAL OIL; GRAPE SEED OIL; APRICOT KERNEL OIL; VITAMIN A PALMITATE; LINOLEIC ACID; LAVENDER OIL; LIMONENE, (+)-; LINALOOL, (+/-)-

4sport skincare anti chafing lotion

Active ingredient:

Lanolin 40%

Purpose

Skin protectant

Uses:

Temporarily protects the skin and prevents chafing, blisters and irritation.

Warnings:

- For external use only. Do not use on: deep or puncture wounds, animal bites, serious burns

- When using this product: use only as directed, avoid contact with eyes or mucous membrane

Stop use and ask a doctor if:

- Redness occurs, irritation develops, symptoms persist for more than 7 days, or clear up and occur again within a few days
- If pregnant or breast-feeding ask a health professional before use.

- Keep out of reach of children. If swallowed get medical help or contact a Poison Control Center (1-800-222-1222) right away.

Direction:

Apply to intact skin before any chafing and blister causing activity. Wash off with mild soap.

Inactive ingredients:

Prunus Dulcis (Sweet Almond) Oil, Mineral Oil, Vitis Vinifera (Grape) Seed Oil, Prunus Armeniaca (Apricot) Seed Oil, Retinyl Palmitate, Linoleic Acid, Parfum/Fragrance, Lavandula Angustifolia (Lavender) Essential oil, Limonene, Linalool

protects and nurtures your skin

The very best from nature

Made with the best ingredients to protect your skin from chafing, blisters and irritation.

No chafing

No blisters

No irritation

No pertroleum

No parabens

No alcohol

Manufactured in EU for:

4SPORT Ltd.,

Ulica Mirka Vadnova 19,

4000 Kranj,Slovenia

www.4sport-skincare.com

Our anti chafing lotion forms a breathable moisture barrier on the skin, to help fight friction. The formulation makes it easy to apply for all-day protection from skin on skin rubbing, chafing from clothing, friction from shoes, protective gear, and other irritants.

- Sweat and water resistant

- Whole body use

- Non-irritating

- Airless ecosolution pump bottle container

Better safe than sorry!